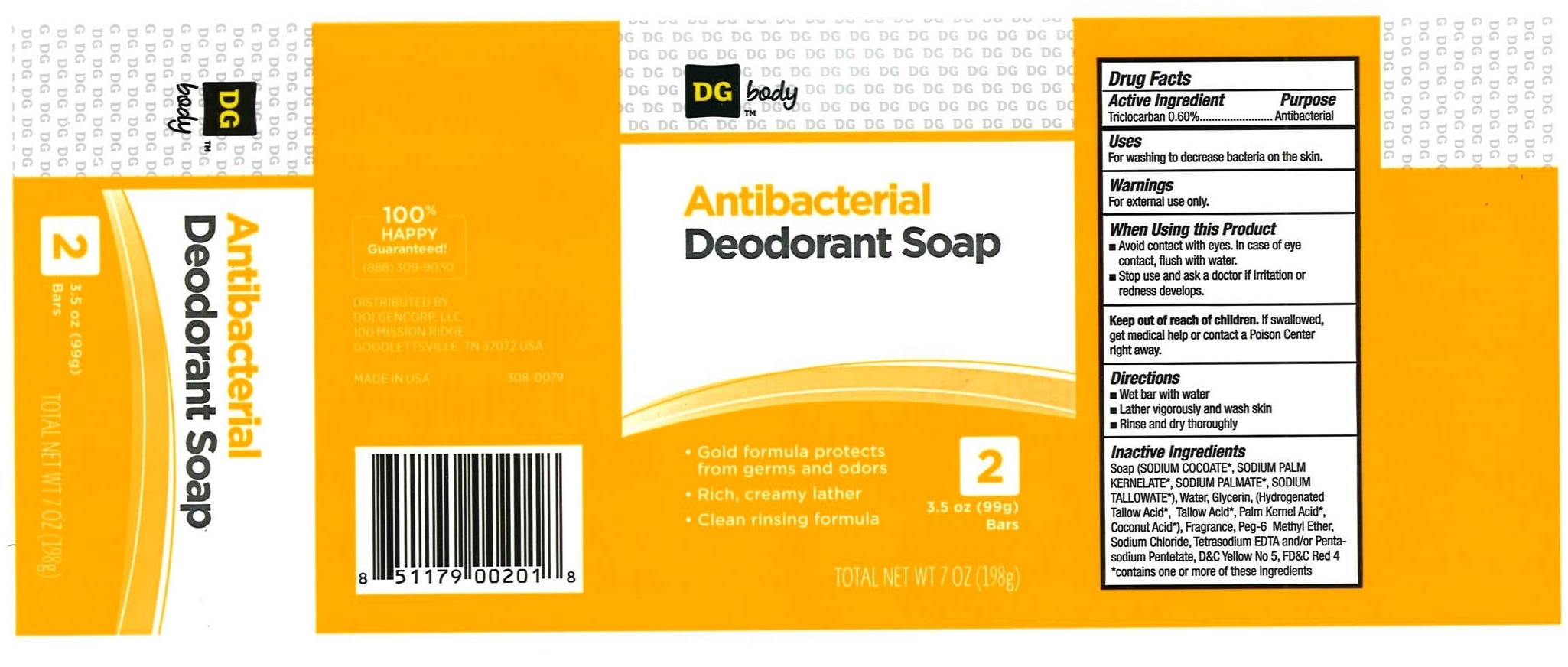 DRUG LABEL: DG Body
NDC: 10889-301 | Form: SOAP
Manufacturer: VVF Kansas Services LLC
Category: otc | Type: HUMAN OTC DRUG LABEL
Date: 20090914

ACTIVE INGREDIENTS: triclocarban 0.60 1/1 1

DG body Antibacterial (triclocarban)

ACTIVE INGREDIENT

Triclocarban 0.60%

PURPOSE

Antibacterial

USES

For washing to decrease bacteria on the skin

WARNINGS

For external use only.

When Using this Product

- Avoid contact with eyes. In case of eye contact, flush with water.
- Stop use and ask a doctor if irritation or redness develops.

Keep out of reach of children. If swallowed, get medical help or contact a Poison Center right away.

DIRECTIONS

- Wet bar with water
- Later vigorously and wash skin
- Rinse and dry thoroughly

INACTIVE INGREDIENTS

Soap (sodium cocoate*, sodium palm kernelate*, sodium palmate*, sodium tallowate*), Water, Glycerin, (Hydrogenated Tallow Acid*, Tallow Acid*, Palm Kernel Acid*, Coconut Acid*), Fragrance, Peg-6 Methyl Ether, Sodium Chloride, Tetrasodium EDTA and / or Pentasodium Pentetate, D+C Yellow No 5, FD+C Red 4

*contains one or more of these ingredients

PRODUCT PACKAGING

DG body (TM)

Antibacterial Deodorant Soap

- Gold formula protects from germs and odors
- Rich, creamy lather
- Clean rinsing formula

2 - 3.5 oz (99g) Bars
TOTAL NET WT 7 OZ (198g)
100% Happy Guaranteed!
(888) 309-9030
DISTRIBUTED BY
DOLGENCORP, LLC
100 MISSION RIDGE
GOODLETTCILLE, TN 37072 USA
MADE IN USA